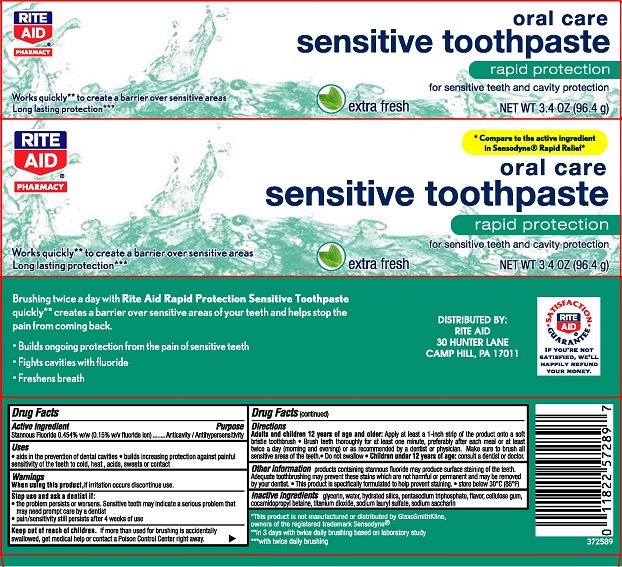 DRUG LABEL: Rite Aid Sensitive
NDC: 11822-6031 | Form: PASTE, DENTIFRICE
Manufacturer: Rite Aid
Category: otc | Type: HUMAN OTC DRUG LABEL
Date: 20251112

ACTIVE INGREDIENTS: STANNOUS FLUORIDE 0.15 g/100 g
INACTIVE INGREDIENTS: SACCHARIN SODIUM; TITANIUM DIOXIDE; SODIUM LAURYL SULFATE; WATER; GLYCERIN; HYDRATED SILICA; COCAMIDOPROPYL BETAINE; SODIUM TRIPOLYPHOSPHATE ANHYDROUS; CARBOXYMETHYLCELLULOSE SODIUM, UNSPECIFIED FORM

5820039 Rite Aid Sensitive Toothpaste Rapid Protection

Drug Facts

Active ingredient

Stannous fluoride 0.454% (0.15% w/v fluoride ion)

Purpose

Anticavity / Antihypersensitivity

Uses

- aids in the prevention of dental cavities
- builds increasing protection against painful sensitivity of the teeth to cold, heat, acids, sweets or contact

Warnings

When using this product, if irritation occurs discontinue use.

Stop use and ask a dentist if:

- the problem persists or worsens. Sensitive teeth may indicate a serious problem that may need prompt care by a dentist.
- pain/sensitivity still persists after 4 weeks of use

Keep out of reach of children. If more than used for brushing is accidentally swallowed, get medical help or contact a Poison Control Center right away.

Directions

Adults and children 12 years of age and older: Apply at least a 1-inch strip of the product onto a soft bristle toothbrush.

- Brush teeth thoroughly for at least one minute, preferably after each meal or at least twice a day (morning and evening) or as recommended by a dentist or physican.
- Make sure to brush all sensitive areas of the teeth.
- Do not swallow
- Children under 12 years of age: consult a dentist or doctor.

Other information

products containing stannous fluoride may produce surface staining of the teeth. Adequate toothbrushing may prevent these stains which are not harmful or permanent and may be removed your dentist.

- This product is specifically formulated to help prevent staining
- store below 30°C (86°F)

INACTIVE INGREDIENT

Inactive ingredients glycerin, water, hydrated silica, pentasodium triphosphate, flavor, cellulose gum, cocamidopropyl betaine, titanium dioxide, sodium lauryl sulfate, sodium saccharin

DISTRIBUTED BY:

RITE AID

30 HUNTER LANE

CAMP HILL, PA 17011

PACKAGE LABEL

RITE AID® PHARMACY

oral care

sensitive toothpaste

rapid protection

for sensitive teeth and cavity protection

extra fresh

NET WT 3.4 OZ (96.4 g)